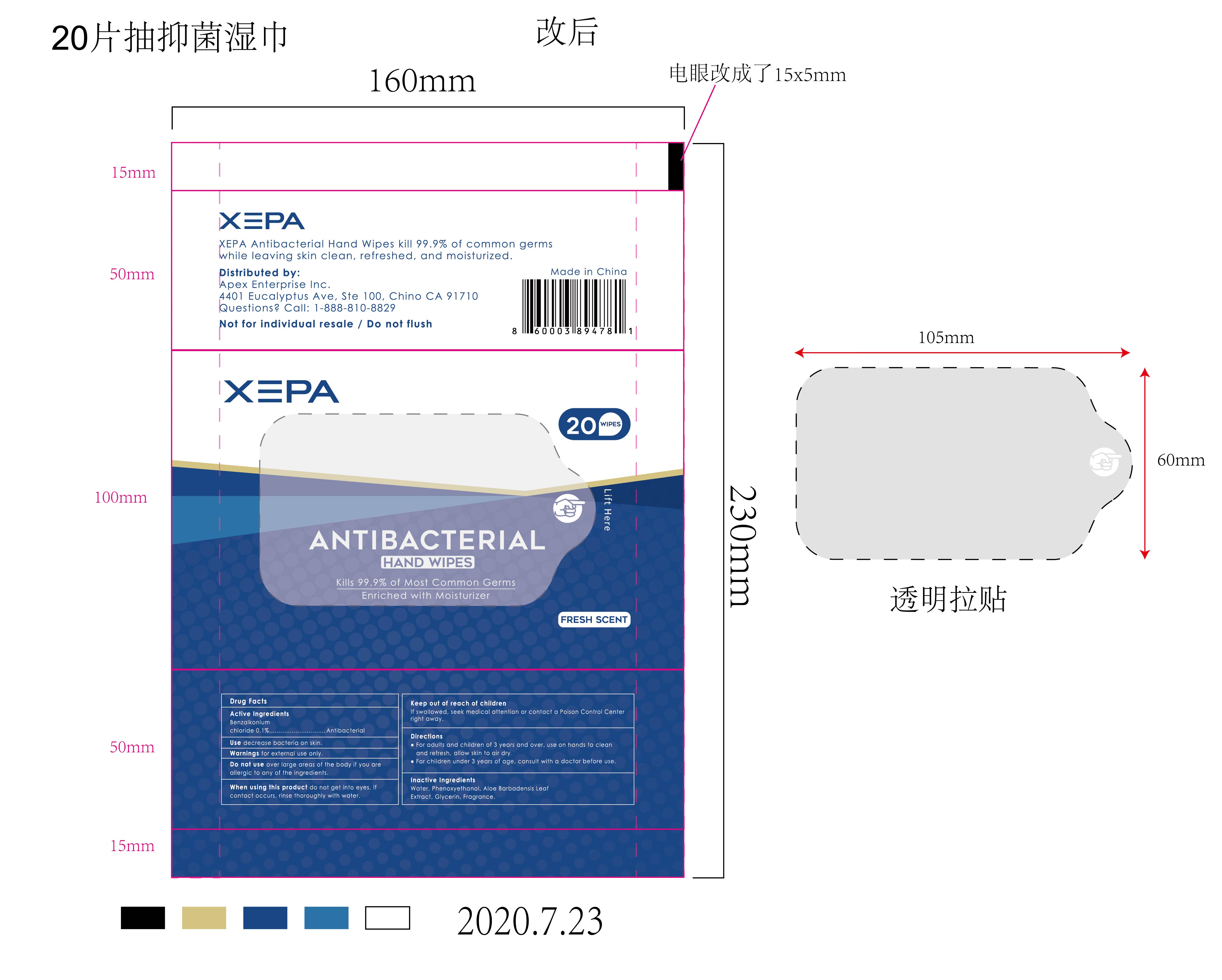 DRUG LABEL: ANTIBACTERIAL HAND WIPES
NDC: 43116-010 | Form: CLOTH
Manufacturer: Shenzhen Shierjie Biological Engineering Co., LTD
Category: otc | Type: HUMAN OTC DRUG LABEL
Date: 20201122

ACTIVE INGREDIENTS: BENZALKONIUM CHLORIDE 0.1 g/100 1
INACTIVE INGREDIENTS: FRAGRANCE LEMON ORC2001060; GLYCERIN; PHENOXYETHANOL; WATER; ALOE VERA LEAF

43116-010
ANTIBACTERIAL HAND WIPES

Active Ingredient(s)

Benzalkonium chloride 0.1%

Purpose

Antibacterial

Use

Use decrease bacteria on skin

Warnings

Warnings for external use only.

Do not use over large areas of the body if you are allergic to any of the ingredients.

When using this product do not get into eyes. If contact occurs, rinse thoroughly with water

STOP USE

/

Keep out of reach of children
If swallowed, seek medical attention or contact a poison control center right away.

Directions

For adults and children of 3 years and over, use on hands to clean and refresh, allow skin to air dry
For children under 3 years of age, consult with a doctor before use

Other information

/

Inactive ingredients

Water, Phenoxyethanol, Aloe Barbadensis Leaf Extract, Glycerin, Fragrance